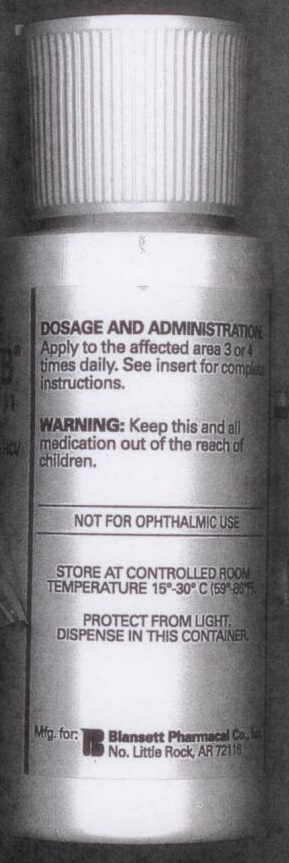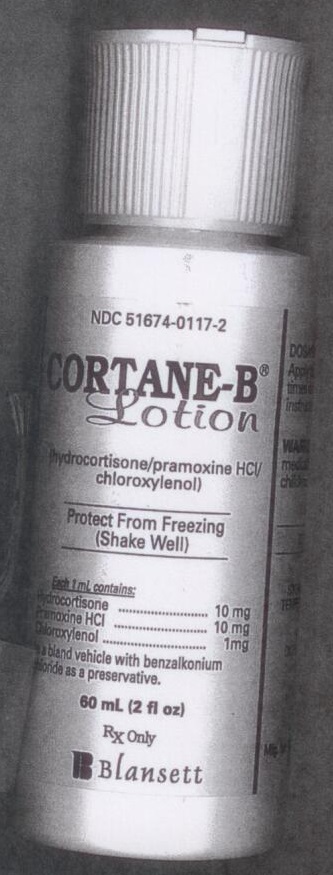 DRUG LABEL: CORTANE-B
NDC: 51674-0117 | Form: LOTION
Manufacturer: BLANSETT PHARMACAL CO
Category: prescription | Type: HUMAN PRESCRIPTION DRUG LABEL
Date: 20170320

ACTIVE INGREDIENTS: HYDROCORTISONE 10 mg/1 mL; PRAMOXINE HYDROCHLORIDE 10 mg/1 mL; CHLOROXYLENOL 1 mg/1 mL
INACTIVE INGREDIENTS: BENZALKONIUM CHLORIDE

CORTANE-B LOTION

DOSAGE AND ADMINISTRATION

APPLY TO THE AFFECTED AREA 3 TO 4 TIMES DAILY. SEE INSERT FOR COMPLETE INSTRUCTIONS.

EACH 1 ML CONTAINS:

HYDROCORTISONE 10 MG

PRAMOXINE HCL 10 MG

CHLOROXYLENOL 1 MG

IS A BLAND VEHICLE WITH BENZALKONIUM CHLORIDE AS A PRESERVATIVE.

WARNING:

KEEP THIS AND ALL MEDICATION OUT OF THE REACH OF CHILDREN.

OTHER SAFETY INFORMATION

PROTECT FROM FREEZING (SHAKE WELL)

NOT FOR OPTHALMIC USE.

STORE AT CONTROLLED ROOM TEMPARATURE 15°-30°C (50°-86°F).

PROTECT FROM LIGHT.

DISPENSE IN CONTAINER.